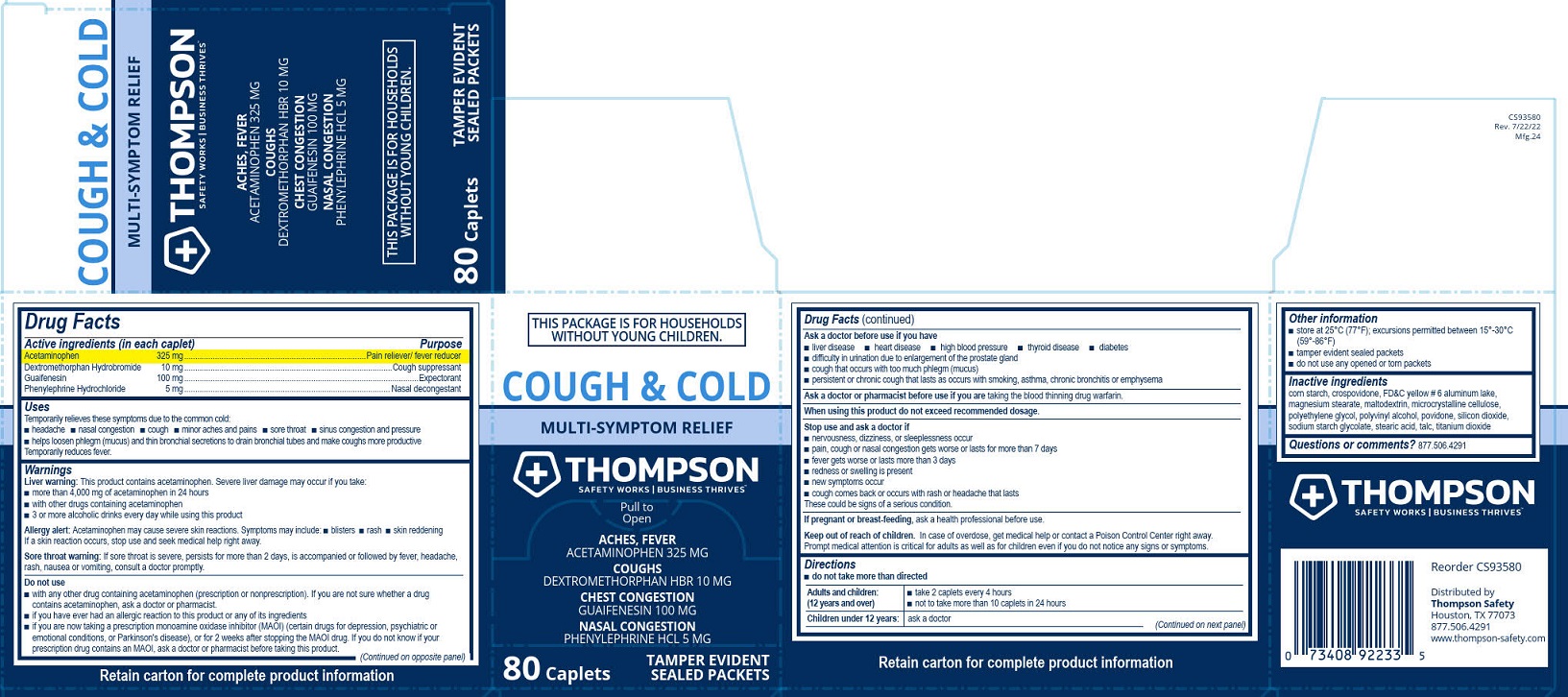 DRUG LABEL: Thompson Cough and Cold Multi-Symptom Relief
NDC: 73408-835 | Form: TABLET, FILM COATED
Manufacturer: Thompson
Category: otc | Type: HUMAN OTC DRUG LABEL
Date: 20260108

ACTIVE INGREDIENTS: GUAIFENESIN 100 mg/1 1; PHENYLEPHRINE HYDROCHLORIDE 5 mg/1 1; ACETAMINOPHEN 325 mg/1 1; DEXTROMETHORPHAN HYDROBROMIDE 10 mg/1 1
INACTIVE INGREDIENTS: STEARIC ACID; FD&C YELLOW NO. 6; POLYETHYLENE GLYCOL, UNSPECIFIED; MAGNESIUM STEARATE; MICROCRYSTALLINE CELLULOSE; TALC; MALTODEXTRIN; POLYVINYL ALCOHOL, UNSPECIFIED; POVIDONE; SILICON DIOXIDE; SODIUM STARCH GLYCOLATE TYPE A POTATO; TITANIUM DIOXIDE; STARCH, CORN; CROSPOVIDONE

Thompson Cough & Cold

Drug Facts

Active ingredients (in each caplet)

Acetaminophen 325 mg

Dextromethorphan HBr 10 mg

Guaifenesin 100 mg

Phenylephrine HCl 5 mg

Purpose

Pain reliever/fever reducer

Cough suppressant

Expectorant

Nasal decongestant

Uses
Temporarily relieves these symptoms due to the common cold:
■ headache
■ nasal congestion
■ cough
■ minor aches and pains
■ sore throat
■ sinus congestion and pressure
■ helps loosen phlegm (mucus) and thin bronchial secretions to drain bronchial tubes and make coughs more productive
Temporarily reduces fever.

Warnings

Liver warning: This product contains acetaminophen. Severe liver damage may occur if you take:

■ more than 4,000 mg of acetaminophen in 24 hours

■ with other drugs containing acetaminophen

■ 3 or more alcoholic drinks every day while using this product

Allergy alert:

Acetaminophen may cause a severe skin reactions. Symptoms may include:

■ blisters

■ rash

■ skin reddening

If a skin reaction occurs, stop use and seek medical help right away.

Sore throat warning:

If sore throat is severe, persists for more than 2 days, is accompanied or followed by fever, headache, rash, nausea or vomiting, consult a doctor promptly.

Do not use
■ with any other drug containing acetaminophen (prescription or nonprescription). If you are not sure whether a drug contains acetaminophen, ask a doctor or pharmacist.
■ if you have ever had an allergic reaction to this product or any of its ingredients
■ if you are now taking a prescription monoamine oxidase inhibitor (MAOI) (certain drugs for depression, psychiatric or emotional conditions, or Parkinson's disease), or for 2 weeks after stopping the MAOI drug. If you do not know if your prescription drug contains an MAOI, ask a doctor or pharmacist before taking this product.

Ask a doctor before use if you have

■ liver disease

■ heart disease

■ high blood pressure

■ thyroid disease

■ diabetes

■ difficulty in urination due to enlargement of the prostate gland

■ cough that occurs with too much phlegm (mucus)

■ persistent or chronic cough that lasts as occurs with smoking, asthma, chronic bronchitis or emphysema

Ask a doctor or pharmacist before use if you are taking the blood thinning drug warfarin.

When using this product do not exceed recommended dosage.

Stop use and ask a doctor if

■ nervousness, dizziness, or sleeplessness occur

■ pain, cough or nasal congestion gets worse or lasts for more than 7 days

■ fever gets worse or lasts more than 3 days

■ redness or swelling is present

■ new symptoms occur

■ cough comes back or occurs with rash or headache that lasts

These could be signs of a serious condition.

PREGNANCY OR BREAST FEEDING

If pregnant or breast-feeding, ask a health professional before use.

Keep out of reach of children. In case of overdose, get medical help or contact a Poison Control Center right away.
Prompt medical attention is critical for adults as well as for children even if you do not notice any signs or symptoms.

Directions

■ do not take more than directed

Adults and children: (12 years and over)

■ take 2 caplets every 4 hours

■ not to take more than 10 caplets in 24 hours

Children under 12 years: ask a doctor

Other information

■ store at 25°C (77°F); excursions permitted between 15°-30°C (59°-86°F)

■ tamper evident sealed packets

■ do not use any opened or torn packets

Inactive ingredients

corn starch, crospovidone, FD&C yellow # 6 aluminum lake, magnesium stearate, maltodextrin, microcrystalline cellulose, polyethylene glycol, polyvinyl alcohol, povidone, silicon dioxide, sodium starch glycolate, stearic acid, talc, titanium dioxide

Questions or comments? 877.506.4291

PACKAGE LABEL

Thompson

Cough & Cold

Multi-Symptom Relief

Safety Works | Business Thrives™

This Package is for Households without Young Children.

Pull to Open

Aches, Fever

Acetaminophen 325 mg

Coughs

Dextromethorphan HBr 10 mg

Chest Congestion

Guaifenesin 100 mg

Nasal Congestion

Phenylephrine HCl 5 mg

80 Caplets

Tamper Evident Sealed Packets